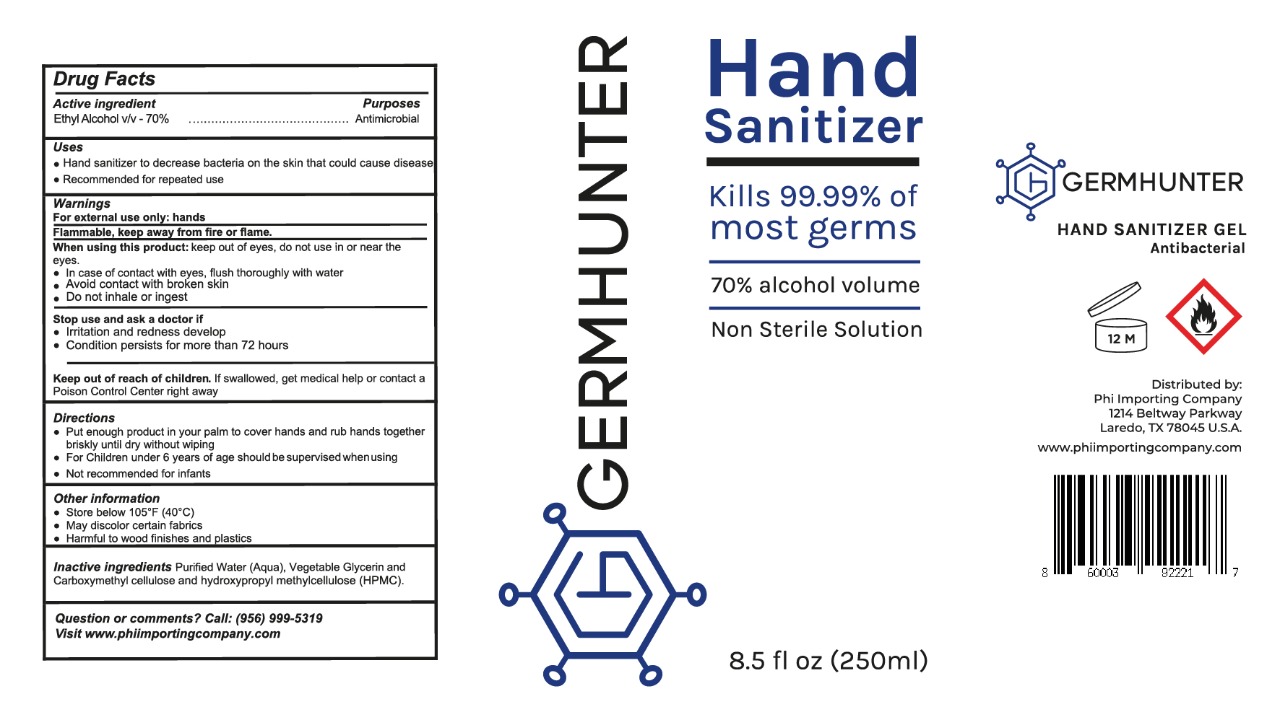 DRUG LABEL: HAND SANITIZER
NDC: 77210-0008 | Form: GEL
Manufacturer: EXPORTADORA IN & OUT S DE RL DE CV
Category: otc | Type: HUMAN OTC DRUG LABEL
Date: 20200610

ACTIVE INGREDIENTS: ALCOHOL 70 mL/100 mL
INACTIVE INGREDIENTS: HYPROMELLOSE 2208 (60000 MPA.S) 0.1 mL/100 mL; CARBOXYMETHYLCELLULOSE 0.1 mL/100 mL; GLYCERIN 0.2 mL/100 mL; WATER 29.6 mL/100 mL

Active ingredient

Ethyl alcohol v/v - 70%

Purposes

Antimicrobial

Uses

- Hand sanitizer to decrease bacteria on the skin that could cause disease

-Recommended for repetead use

Warnings

For external use only: hands

Flammable, keep away from fire and flame

When using this product

keep out of eyes, do not use in or near the eyes.

- In case of contact with eyes, flush thorougly with water

- Avoid contact with broken skin

- Do not inhale or ingest

When using this product

keep out of eyes, do not use in or near the eyes.

- In case of contact with eyes, flush thorougly with water

- Avoid contact with broken skin

- Do not inhale or ingest

Stop use and ask a doctor if

- Irritation and redness develop

- Condition persists for more than 72 hours

Keep out of reach of children

If swallowed, get medical help or contact a poison contro center right away

Directions

¨-Put enough product in your palm to cover hands and rub hands together briskly until dry without wiping

-For children under 6 years of age should be supervised when using

-Not recommended for infants

Other information

-Store below 105F (40C)

-May discolour certain fabrics

-Harmful to wood finishes and plastics

Inactive ingredients

Purified water (aqua), vegetable glycerin and carboxymethyl cellulose and hydrocypropyl methylcellulose (HPMC)

Question or comments

call: (956) 999-5319

visit www.phiimportingcompany.com

PRINCIPAL DISPLAY

HAND SANITIZER

KILLS 99.9% OF MOST GERMS

70% ALCOHOL VOLUME

NON STERILE SOLUTION

8.5 FL OZ (250 ML)